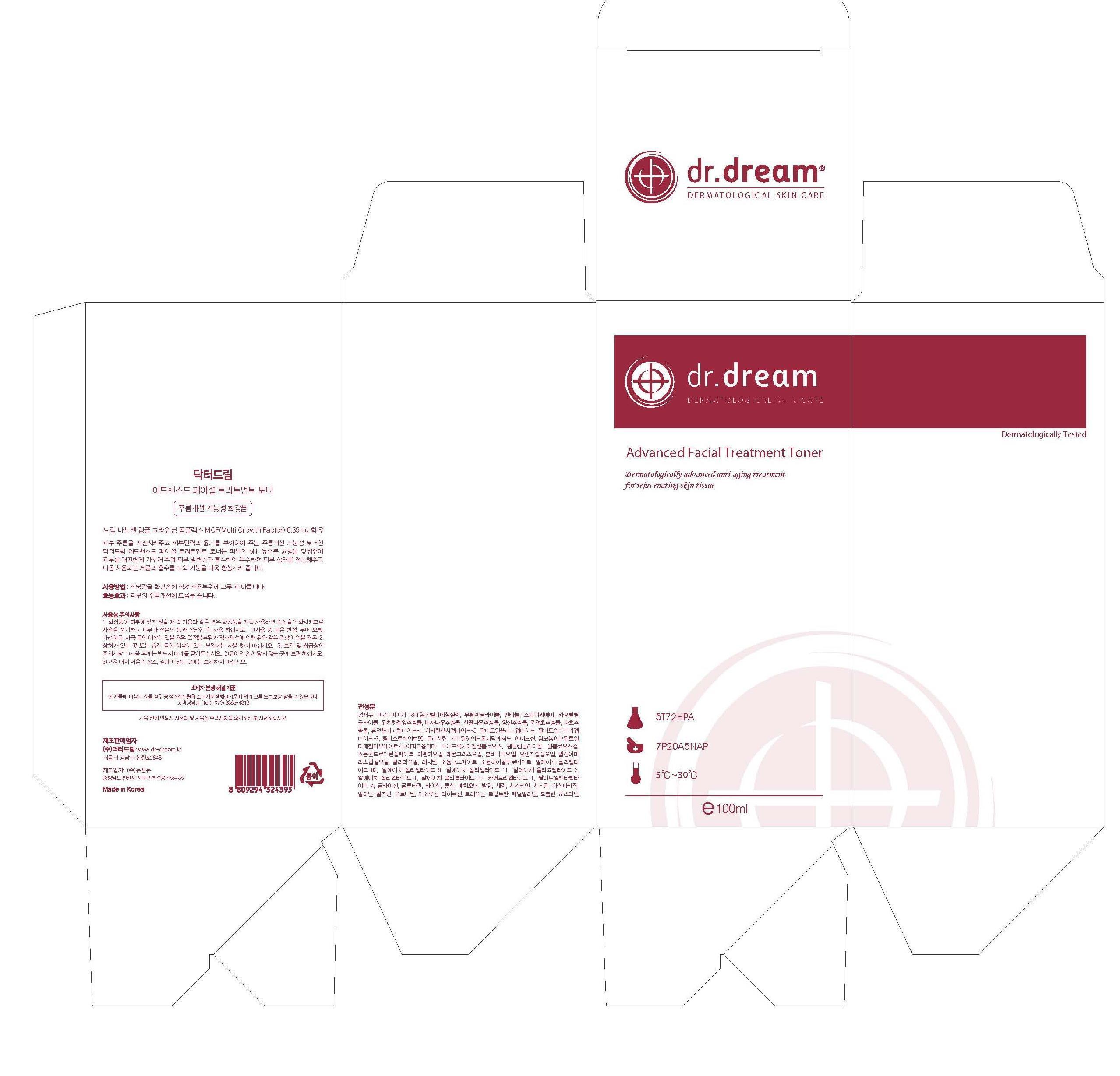 DRUG LABEL: Dr. Dream Advanced Facial Treatment Toner
                
NDC: 53077-1001 | Form: LIQUID
Manufacturer: Dr. Dream Inc
Category: otc | Type: HUMAN OTC DRUG LABEL
Date: 20120824

ACTIVE INGREDIENTS: WITCH HAZEL 0.1 mg/100 mL
INACTIVE INGREDIENTS: BIS-PEG-18 METHYL ETHER DIMETHYL SILANE; BUTYLENE GLYCOL; PANTHENOL; SODIUM PYRROLIDONE CARBOXYLATE; CAPRYLYL GLYCOL; TORREYA NUCIFERA WHOLE; ROSA DAMASCENA FLOWER OIL; MUSA BASJOO WHOLE; ACETYL HEXAPEPTIDE-8; PALMITOYL OLIGOPEPTIDE; PALMITOYL TETRAPEPTIDE-7; POLYSORBATE 80; GLYCERIN; CAPRYLHYDROXAMIC ACID; ADENOSINE; AMMONIUM ACRYLOYLDIMETHYLTAURATE/VP COPOLYMER; NEOPENTYL GLYCOL; CARBOXYMETHYLCELLULOSE SODIUM; SODIUM CHONDROITIN SULFATE (PORCINE; 5500 MW); LAVANDULA ANGUSTIFOLIA FLOWERING TOP; CYMBOPOGON SCHOENANTHUS OIL; ABIES SIBIRICA LEAF OIL; ORANGE; AMYRIS BALSAMIFERA OIL; CLARY SAGE OIL; LECITHIN, SOYBEAN; SODIUM PHOSPHATE; HYALURONATE SODIUM; THIOREDOXIN; PREZATIDE COPPER; PALMITOYL PENTAPEPTIDE-4; GLYCINE; GLUTAMINE; LYSINE; LEUCINE; METHIONINE; VALINE; SERINE; CYSTEINE; CYSTINE; ASPARAGINE; ALANINE; ARGININE; ORNITHINE; ISOLEUCINE; TYROSINE; THREONINE; TRYPTOPHAN; PHENYLALANINE; PROLINE; HISTIDINE

Drug Facts

ACTIVE INGREDIENT

witch hazel

INACTIVE INGREDIENT

bis-PEG-18 methyl ether dimethyl silane, butylene glycol, panthenol, sodium PCA, caprylyl glycol, torreya nucifera extract, cornus kousa extract, rosa multiflora fruit extract, chloranthus glaber extract, musa basjoo extract, musa basjoo extract, rh-oligopeptide-1, acetyl hexapeptide=8, palmitoyl oligopeptice, palmitoyl tetrapeptide-7, polysorbate 80, glycerin, caprylhydroxamic acid, adenosine, ammonium acryloyldimethyltaurate, hydroxyethylcellulose, pentylene glycol, cellulose gum, sodium chondroitin sulfate, lavandula angustifolia oil, cymbopogon schoenanthus oil, abies sibirica oil, citrus auratium dulcis peel oil, amyris balsamifera bark oil, salvia sclarea oil, lecithin, sodium phosphate, sodium hyaluronate, rh-polypeptide-60, rh-polypeptide-9, rh-polypeptide-11, rh-polypeptide-2, rh-polypeptide-1, rh-polypeptide-10, copper tripeptide-1, palmitoyl pentapeptide-4, glycine, glutamine, lysine, leucine, methionine, valine, serine, cysteine, cystine, asparagine, alanine, arginine, ornithine, isoleucine,tyrosine, threonine, tryptophan, phenylalanine, proline, histidine

PURPOSE

anti wrinkle

keep out of reach of the children

INDICATIONS AND USAGE

after cleaning up your face with clean water apply proper amount to your skin and massage a few minutes

When using this product
- keep out of eyes, ears, and mouth. If contact occurs, rinse with plenty of cold water right away and contact a physician. If swallowing, drink plenty of water and contact a physician

DOSAGE AND ADMINISTRATION

for external use only